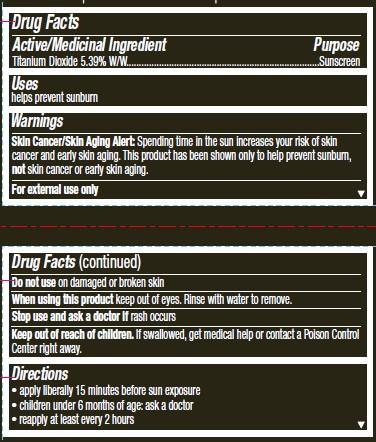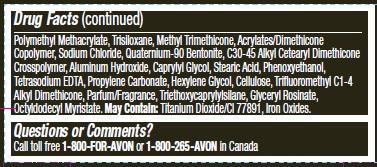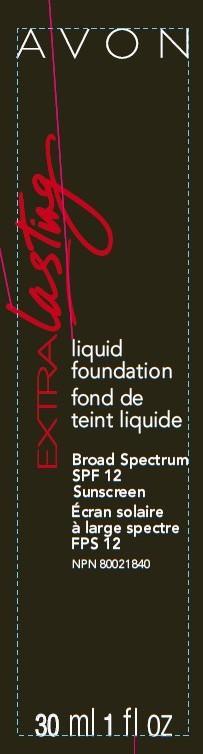 DRUG LABEL: Extralasting
NDC: 10096-0232 | Form: LOTION
Manufacturer: New Avon LLC
Category: otc | Type: HUMAN OTC DRUG LABEL
Date: 20160212

ACTIVE INGREDIENTS: TITANIUM DIOXIDE 53.9 mg/1 mL

Active/Medicinal Ingredient
Titanium Dioxide 5.39% W/W............

Purpose
......................................Sunscreen

Uses
helps prevent sunburn

Warnings

Skin Cancer/Skin Aging Alert: Spending time in the sun increases your risk of skin cancer and early skin aging. This product has been shown only to help prevent sunburn, not skin cancer or early skin aging.

For external use only

Do not use on damaged or broken skin

When using this product keep out of eyes. Rinse with water to remove.

Stop use and ask a doctor if rash occurs

Keep out of reach of children. If swallowed, get medical help or contact a Poison Control Center right away.

Directions

• apply liberally 15 minutes before sun exposure
• children under 6 months of age: ask a doctor
• reapply at least every 2 hours

• use a water resistant sunscreen if swimming or sweating

Other information
• protect the product in this container from excessive heat and direct sun

INACTIVE INGREDIENT

Inactive/non-medicinal ingredients: Water/Eau, Cyclopentasiloxane, Dimethicone, Dipropylene Glycol, Glycerin, PEG-10 Dimethicone, Nylon-12, Polymethyl Methacrylate, Trisiloxane, Methyl Trimethicone, Acrylates/Dimethicone Copolymer, Sodium Chloride, Quaternium-90 Bentonite, C30-45 Alkyl Cetearyl Dimethicone Crosspolymer, Aluminum Hydroxide, Caprylyl Glycol, Stearic Acid, Phenoxyethanol, Tetrasodium EDTA, Propylene Carbonate, Hexylene Glycol, Cellulose, Trifluoromethyl C1-4 Alkyl Dimethicone, Parfum/Fragrance, Triethoxycaprylylsilane, Glyceryl Rosinate, Octyldodecyl Myristate. May Contain: Titanium Dioxide/CI 77891, Iron Oxides.

Questions or Comments?
Call toll free 1-800-FOR-AVON or 1-800-265-AVON in Canada